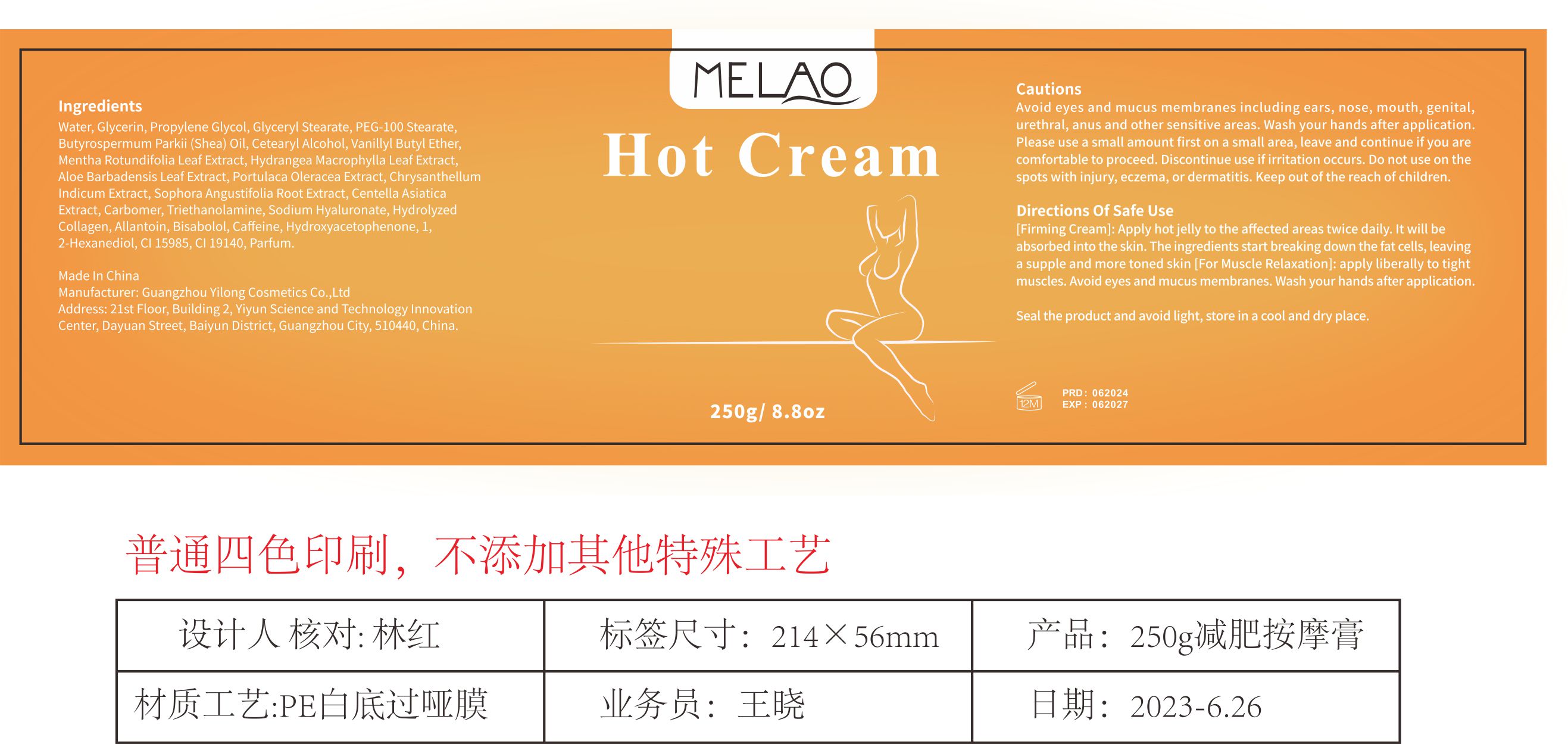 DRUG LABEL: MELAO Hot Cream
NDC: 74458-029 | Form: CREAM
Manufacturer: Guangzhou Yilong Cosmetics Co., Ltd
Category: otc | Type: HUMAN OTC DRUG LABEL
Date: 20241010

ACTIVE INGREDIENTS: CAFFEINE 0.3 g/100 g; VANILLYL BUTYL ETHER 3 g/100 g
INACTIVE INGREDIENTS: TROLAMINE; SOPHORA FLAVESCENS ROOT; HYALURONATE SODIUM; SHEANUT OIL; FD&C YELLOW NO. 5; PURSLANE; CHRYSANTHELLUM INDICUM TOP; GLYCERIN; PEG-100 STEARATE; MENTHA X ROTUNDIFOLIA LEAF; CARBOMER HOMOPOLYMER, UNSPECIFIED TYPE; ALLANTOIN; .ALPHA.-BISABOLOL, (+)-; PARFUMIDINE; PROPYLENE GLYCOL; CENTELLA ASIATICA TRITERPENOIDS; HYDROXYACETOPHENONE; 1,2-HEXANEDIOL; WATER; CETOSTEARYL ALCOHOL; FD&C YELLOW NO. 6; GLYCERYL MONOSTEARATE; ALOE VERA LEAF; HYDRANGEA MACROPHYLLA LEAF

MELAO Hot Cream

ACTIVE INGREDIENT

Vanillyl Butyl Ether

Caffeine

INACTIVE INGREDIENT

Water

Glycerin

Propylene Glycol

Glyceryl Stearate

PEG-100 Stearate

Butyrospermum Parkii (Shea) Oil

Cetearyl Alcohol

Mentha Rotundifolia Leaf Extract

Hydrangea Macrophylla Leaf Extract

Aloe Barbadensis Leaf Extract

Portulaca Oleracea Extract

Chrysanthellum Indicum Extract

Sophora Angustifolia Root Extract

Centella Asiatica Extract

Carbomer

Triethanolamine

Sodium Hyaluronate

Hydrolyzed Collagen

Allantoin

Bisabolol

Hydroxyacetophenone

1,2-Hexanediol

CI 15985

CI 19140

Parfum

INDICATIONS AND USAGE

[Firming Cream]： Apply hot jelly to the affected areas twice daily. lt will be absorbed into the skin. The ingredients start breaking down the fat cells, leaving a supple and more toned skin.

[For Muscle Relaxationl]：apply liberally to tight muscles. Avoid eyes and mucus membranes. Wash your hands after application.

PURPOSE

Promotes fat burning.

WARNINGS

For external use only.

Stop use and ask a doctor if rash occurs.

Do not use on damaged or broken skin.

When using this product keep out of eyes. Rinse with water to remove.

Keep out of reach of children. If swallowed, get medical help or contact a Poison Control Center right away.

DOSAGE AND ADMINISTRATION

[Firming Cream]: Apply hot jelly to the affected areas twice daily. it will be absorbed into the skin. The ingredients start breaking down the fat cells, leaving a supple and more toned skin.

[For Muscle Relaxation]: apply liberally to tight muscles. Avoid eyes and mucus membranes. Wash your hands after application.